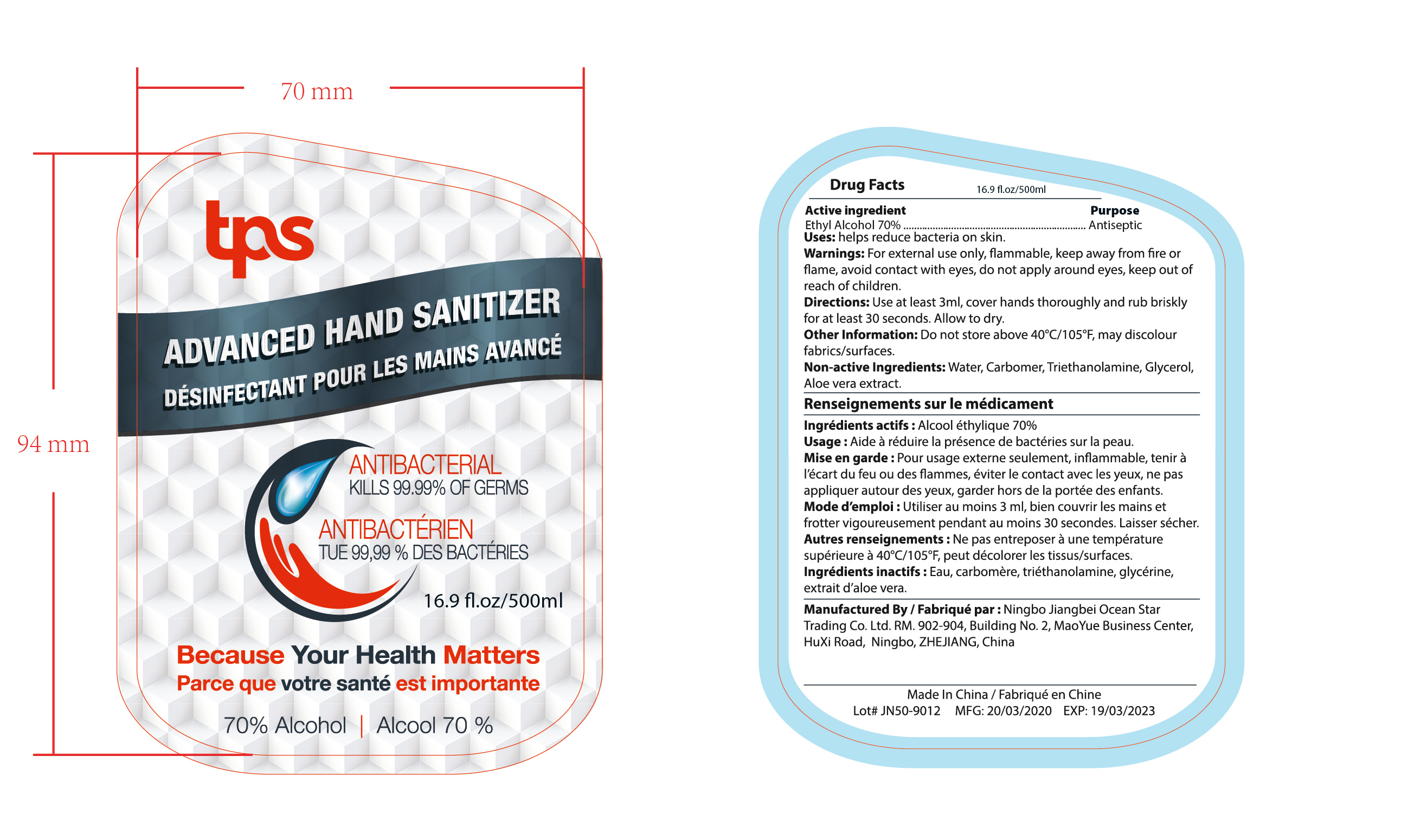 DRUG LABEL: HAND SANITIZER
NDC: 47993-274 | Form: GEL
Manufacturer: NINGBO JIANGBEI OCEAN STAR TRADING CO.,LTD
Category: otc | Type: HUMAN OTC DRUG LABEL
Date: 20201105

ACTIVE INGREDIENTS: ALCOHOL 70 g/112 mL
INACTIVE INGREDIENTS: ALOE VERA LEAF; WATER; CARBOMER 940; TRIETHANOLAMINE BENZOATE; GLYCERIN

47993-274

Active ingredients

Ethyl Alcohol 70%

PURPOSE

Antiseptic

Uses：

helps reduce bacteria on skin.

Warnings:

For external use only，flammable，keep away from fire or flame，avoid contact with eyes，do not apply around eyes，keep out of reach of children.

Keep out of reach of children.

Directions:

Use at least 3ml，cover hands thoroughly and rub briskly for at least 30 seconds. Allow to dry.

INACTIVE INGREDIENT

Non-active Ingredients: Water,Carbomer,Triethanolamine,Glycerol,Aloe vera extract.

Other Information: Do not store above 40ºC/105ºF, may discolour fabrics/surfaces.